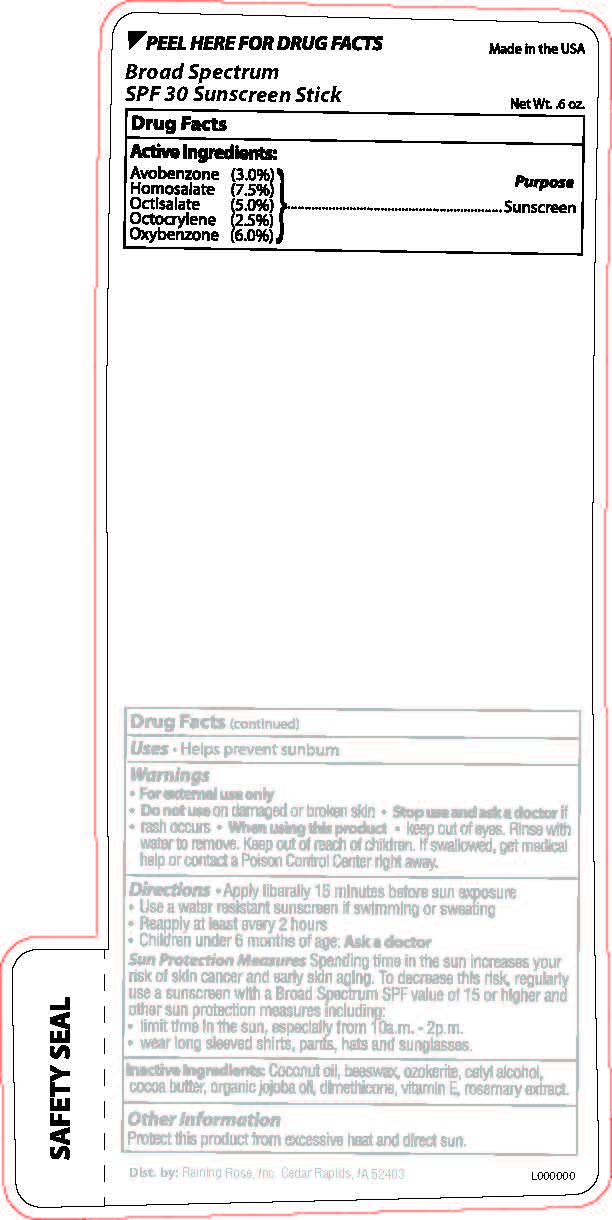 DRUG LABEL: Broad Spectrum SPF 30 Sun Stick
NDC: 65692-0518 | Form: STICK
Manufacturer: Raining Rose, Inc
Category: otc | Type: HUMAN OTC DRUG LABEL
Date: 20231023

ACTIVE INGREDIENTS: OCTISALATE 0.09 g/17 g; AVOBENZONE 0.51 g/17 g; OCTOCRYLENE 0.43 g/17 g; OXYBENZONE 1.02 g/17 g; HOMOSALATE 1.28 g/17 g
INACTIVE INGREDIENTS: COCONUT OIL; CERESIN; TOCOPHEROL; ROSEMARY; WHITE WAX; CETYL ALCOHOL; COCOA BUTTER; ALOE VERA LEAF; JOJOBA OIL

BS SPF 30 Sun Stick

Active Ingredients

Avobenzone 3.0%

Homosalate 7.5%

Octisalate 5.0%

Octocrylene 2.5%

Oxybenzone 6.0%

Purpose

Sunscreen

Warnings

For external use only

Do not use

on damaged or broken skin.

Stop Use and ask a doctor if

Rash Occurs

When Using this Product

Keep out of eyes. Rinse well with water to remove.

Keep out of reach of children

If swallowed, get medical help or contact a Poison Control Center right away.

Directions

Apply liberally 15 minutes before sun exposure

Use a water resistant sunscreen if swimming or sweating

Reapply at least every 2 hours
Children under 6 months of age: Ask a doctor

Inactive ingredients:

Coconut oil, beeswax, ozokerite, cetyl alcohol, cocoa butter, organic jojoba oil, dimethicone, vitamin E, rosemary extract.

DOSAGE AND ADMINISTRATION

Apply liberally 15 minutes before sun exposure

INDICATIONS AND USAGE

Helps prevent sunburn